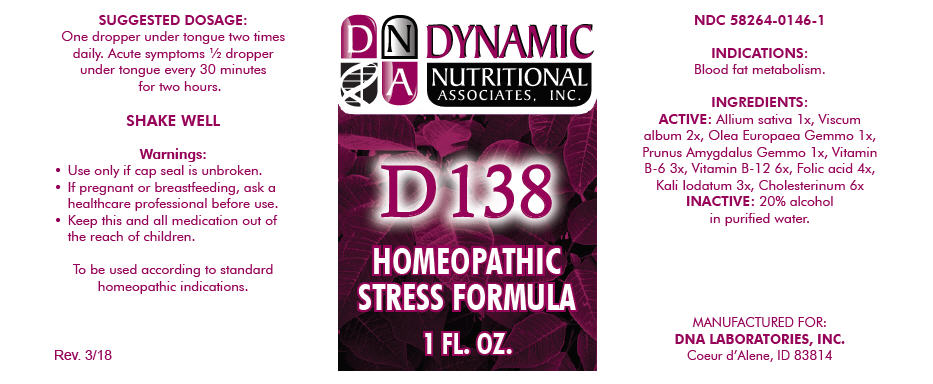 DRUG LABEL: D-138
NDC: 58264-0146 | Form: SOLUTION
Manufacturer: DNA Labs, Inc.
Category: homeopathic | Type: HUMAN OTC DRUG LABEL
Date: 20250113

ACTIVE INGREDIENTS: GARLIC 1 [hp_X]/1 mL; VISCUM ALBUM FRUITING TOP 2 [hp_X]/1 mL; OLEA EUROPAEA FLOWER BUD 1 [hp_X]/1 mL; PRUNUS DULCIS FLOWER 1 [hp_X]/1 mL; PYRIDOXINE HYDROCHLORIDE 3 [hp_X]/1 mL; CYANOCOBALAMIN 6 [hp_X]/1 mL; FOLIC ACID 4 [hp_X]/1 mL; POTASSIUM IODIDE 3 [hp_X]/1 mL; CHOLESTEROL 6 [hp_X]/1 mL
INACTIVE INGREDIENTS: ALCOHOL; WATER

D-138

NDC 58264-0146-1

INDICATIONS

PURPOSE

Blood fat metabolism.

INGREDIENTS

ACTIVE

Allium sativa 1x, Viscum album 2x, Olea Europaea Gemmo 1x, Prunus Amygdalus Gemmo 1x, Vitamin B-6 3x, Vitamin B-12 6x, Folic acid 4x, Kali Iodatum 3x, Cholesterinum 6x

INACTIVE

20% alcohol in purified water.

SUGGESTED DOSAGE

One dropper under tongue two times daily. Acute symptoms ½ dropper under tongue every 30 minutes for two hours.

STORAGE AND HANDLING

SHAKE WELL

Warnings

- Use only if cap seal is unbroken.

PREGNANCY OR BREAST FEEDING

- If pregnant or breastfeeding, ask a healthcare professional before use.

KEEP OUT OF REACH OF CHILDREN

- Keep this and all medication out of the reach of children.

To be used according to standard homeopathic indications.

PRINCIPAL DISPLAY PANEL - 1 FL. OZ. Bottle Label

DYNAMIC
NUTRITIONAL
ASSOCIATES, INC.

D 138

HOMEOPATHIC
STRESS FORMULA

1 FL. OZ.